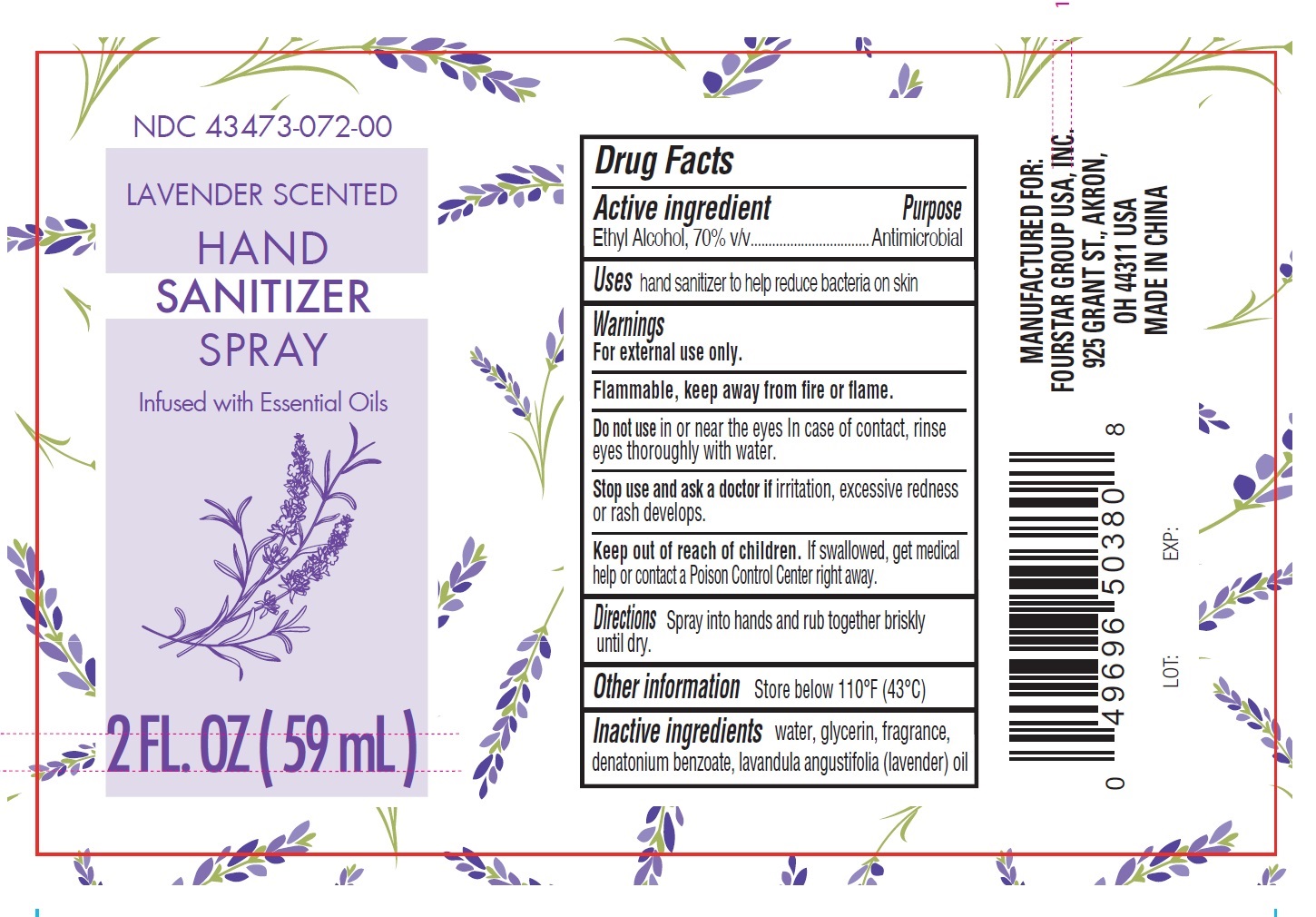 DRUG LABEL: B-Pure Lavender Scented Hand Sanitizer
NDC: 80684-095 | Form: LIQUID
Manufacturer: Fourstar Group USA, Inc.
Category: otc | Type: HUMAN OTC DRUG LABEL
Date: 20231130

ACTIVE INGREDIENTS: ALCOHOL 70 mL/100 mL
INACTIVE INGREDIENTS: WATER; GLYCERIN; DENATONIUM BENZOATE; LAVENDER OIL

B-Pure Lavender Scented Hand Sanitizer Spray

Active ingredient

Ethyl Alcohol, 70% v/v

Purpose

Antimicrobial

Uses

hand sanitizer to help reduce bacteria on skin

Warnings

For external use only.

Flammable, keep away from fire or flame.

Do not use

in or near the eyes in case of contact, rinse eyes thoroughly with water.

Stop use and ask a doctor if

irritation, excessive redness or rash develops.

Keep out of reach of children.

If swallowed, get medical help or contact a Poison Control Center right away.

Directions

Spr ay into hands and rub together briskly until dry.

Other information

Store below 110°F (43°C)

Inactive ingredients

Water, glycerin, fragrance, denatonium benzoate, lavandula angustifolia (lavender) oil